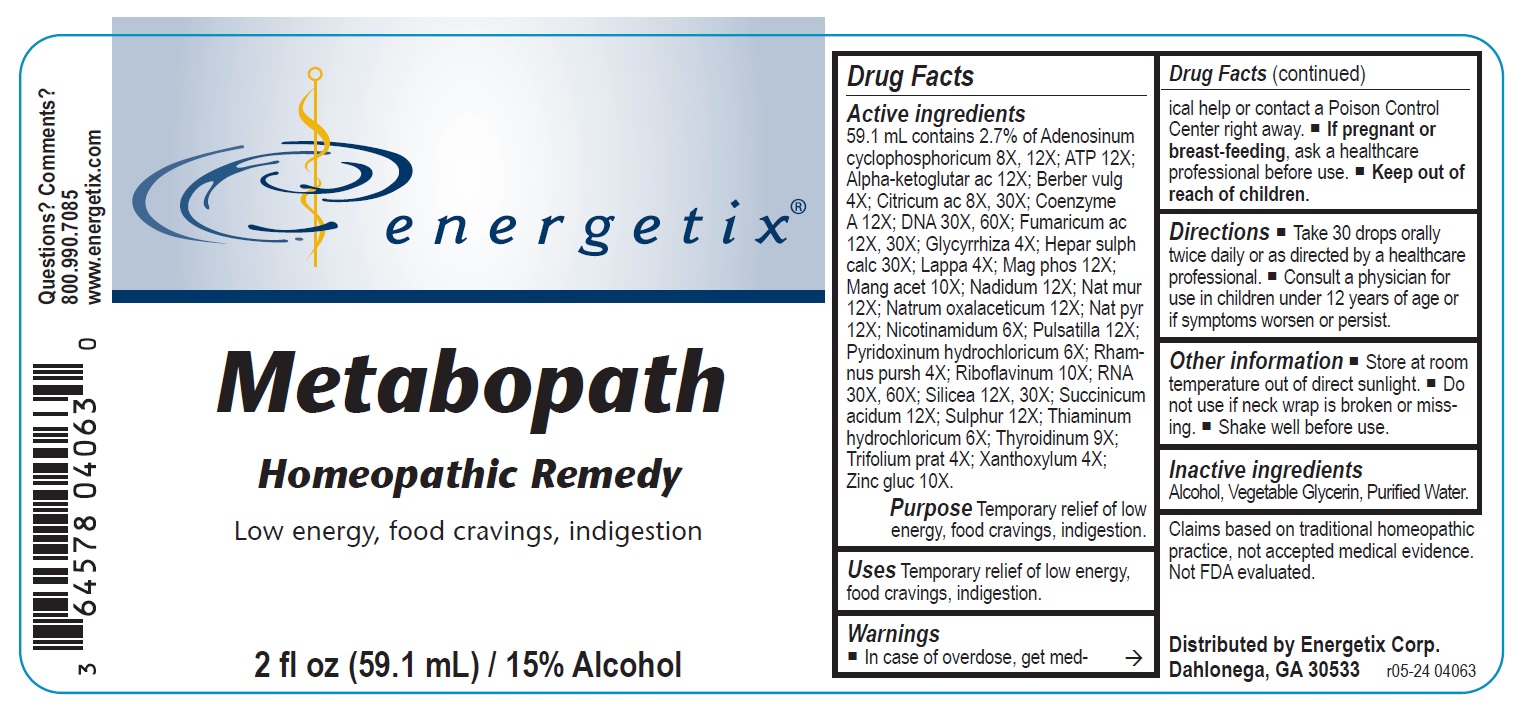 DRUG LABEL: Metabopath
NDC: 64578-0102 | Form: LIQUID
Manufacturer: Energetix Corporation
Category: homeopathic | Type: HUMAN OTC DRUG LABEL
Date: 20241120

ACTIVE INGREDIENTS: ADENOSINE CYCLIC PHOSPHATE 8 [hp_X]/1 mL; .ALPHA.-KETOGLUTARIC ACID 12 [hp_X]/1 mL; ADENOSINE TRIPHOSPHATE DISODIUM 12 [hp_X]/1 mL; BERBERIS VULGARIS ROOT BARK 4 [hp_X]/1 mL; ANHYDROUS CITRIC ACID 8 [hp_X]/1 mL; COENZYME A 12 [hp_X]/1 mL; HERRING SPERM DNA 30 [hp_X]/1 mL; FUMARIC ACID 12 [hp_X]/1 mL; GLYCYRRHIZA GLABRA 4 [hp_X]/1 mL; CALCIUM SULFIDE 30 [hp_X]/1 mL; ARCTIUM LAPPA ROOT 4 [hp_X]/1 mL; MAGNESIUM PHOSPHATE, DIBASIC 12 [hp_X]/1 mL; MANGANESE ACETATE TETRAHYDRATE 10 [hp_X]/1 mL; NADIDE 12 [hp_X]/1 mL; SODIUM CHLORIDE 12 [hp_X]/1 mL; SODIUM DIETHYL OXALACETATE 12 [hp_X]/1 mL; SODIUM PYRUVATE 12 [hp_X]/1 mL; NIACINAMIDE 6 [hp_X]/1 mL; PULSATILLA VULGARIS 12 [hp_X]/1 mL; PYRIDOXINE HYDROCHLORIDE 6 [hp_X]/1 mL; FRANGULA PURSHIANA BARK 4 [hp_X]/1 mL; RIBOFLAVIN 10 [hp_X]/1 mL; SACCHAROMYCES CEREVISIAE RNA 30 [hp_X]/1 mL; SILICON DIOXIDE 12 [hp_X]/1 mL; SUCCINIC ACID 12 [hp_X]/1 mL; SULFUR 12 [hp_X]/1 mL; THIAMINE HYDROCHLORIDE 6 [hp_X]/1 mL; THYROID, BOVINE 9 [hp_X]/1 mL; TRIFOLIUM PRATENSE FLOWER 4 [hp_X]/1 mL; ZANTHOXYLUM AMERICANUM BARK 4 [hp_X]/1 mL; ZINC GLUCONATE 10 [hp_X]/1 mL
INACTIVE INGREDIENTS: WATER; GLYCERIN; ALCOHOL

Metabopath

ACTIVE INGREDIENT

Active ingredients59.1 mL contains 2.7% of: Adenosinum cyclophosphoricum 8X, 12X; ATP 12X; Alpha-ketoglutar ac 12X; Berber vulg
4X; Citricum ac 8X, 30X; Coenzyme A 12X; DNA 30X, 60X; Fumaricum ac 12X, 30X; Glycyrrhiza 4X; Hepar sulph calc 30X; Lappa 4X; Mag phos
12X; Mang acet 10X; Nadidum 12X; Nat mur 12X; Natrum oxalaceticum 12X; Nat pyr 12X; Nicotinamidum 6X; Pulsatilla 12X; Pyridoxinum hydrochloricum 6X; Rhamnus pursh 4X; Riboflavinum 10X; RNA 30X, 60X; Silicea 12X, 30X; Succinicum acidum 12X; Sulphur 12X; Thiaminum hydrochloricum 6X; Thyroidinum 9X;Trifolium prat 4X; Xanthoxylum 4X; Zinc gluc 10X.

Claims based on traditional homeopathic practice, not accepted medical evidence. Not FDA evaluated.

INDICATIONS AND USAGE

UsesTemporary relief of low energy, food cravings, indigestion.

Warnings

- In case of overdose, get medical help or contact a Poison Control Center right away.
- If pregnant or breast-feeding, ask a healthcare professional before use.

- Keep out of reach of children.

Directions

- Take 30 drops orally twice daily or as directed by a healthcare professional.
- Consult a physician for use in children under 12 years of age or if symptoms worsen or persist

Other information

- Store at room temperature out of direct sunlight.
- Do not use if neck wrap is broken or missing.
- Shake well before use.

Inactive ingredients Alcohol, Vegetable Glycerin, Purified Water.

QUESTIONS

Distributed by Energetix Corp.
Dahlonega, GA 30533
Questions? Comments?

800.990.7085

www.energetix.com

PACKAGE LABEL

energetix

Metabopath

Homeopathic Remedy
Low energy, food cravings, indigestion.

2 fl oz (59.1 mL) / 15% Alcohol

PURPOSE

Purpose Temporary relief of low energy, food cravings, indigestion.